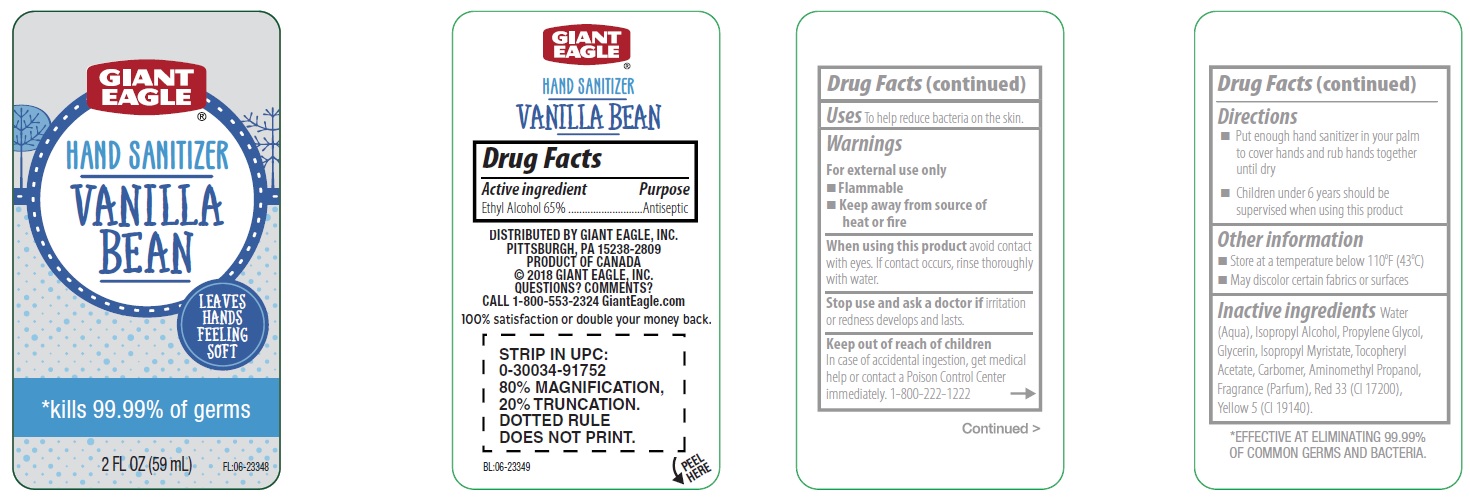 DRUG LABEL: Giant Eagle Vanilla Bean Hand Sanitizer
NDC: 63148-014 | Form: LIQUID
Manufacturer: Apollo Health and Beauty Care Inc.
Category: otc | Type: HUMAN OTC DRUG LABEL
Date: 20180618

ACTIVE INGREDIENTS: ALCOHOL 650 mg/1 mL
INACTIVE INGREDIENTS: WATER; ISOPROPYL ALCOHOL; PROPYLENE GLYCOL; GLYCERIN; ISOPROPYL MYRISTATE; .ALPHA.-TOCOPHEROL ACETATE, DL-; CARBOMER 934; AMINOMETHYLPROPANOL; D&C RED NO. 33; FD&C YELLOW NO. 5

Drug Facts

Active ingredient

Ethyl Alcohol 65%

Purpose

Antiseptic

Uses

To help reduce bacteria on the skin.

Warnings

For external use only

- Flammable
- Keep away from source of heat or fire

When using this product

avoid contact with eyes. If contact occurs, rinse thoroughly with water.

Stop use and ask a doctor if

irritation or redness develops and lasts.

Keep out of reach of children.

In case of accidental ingestion, get medical help or contact a Poison Control Center immediately. 1-800-222-1222

Directions

- Put enough hand sanitizer in your palm to cover hands and rub hands together until dry.
- Children under 6 years should be supervised when using this product.

Other information

- Store at a temperature below 110ºC (43ºC)
- May discolor certain fabrics or surfaces

Inactive ingredients

Water (Aqua), Isopropyl Alcohol, Propylene Glycol, Glycerin, Isopropyl Myristate, Tocopheryl Acetate, Carbomer, Aminomethyl Propanol, Fragrance (Parfum), Red 33 (CI 17200), Yellow 5 (CI 19140).